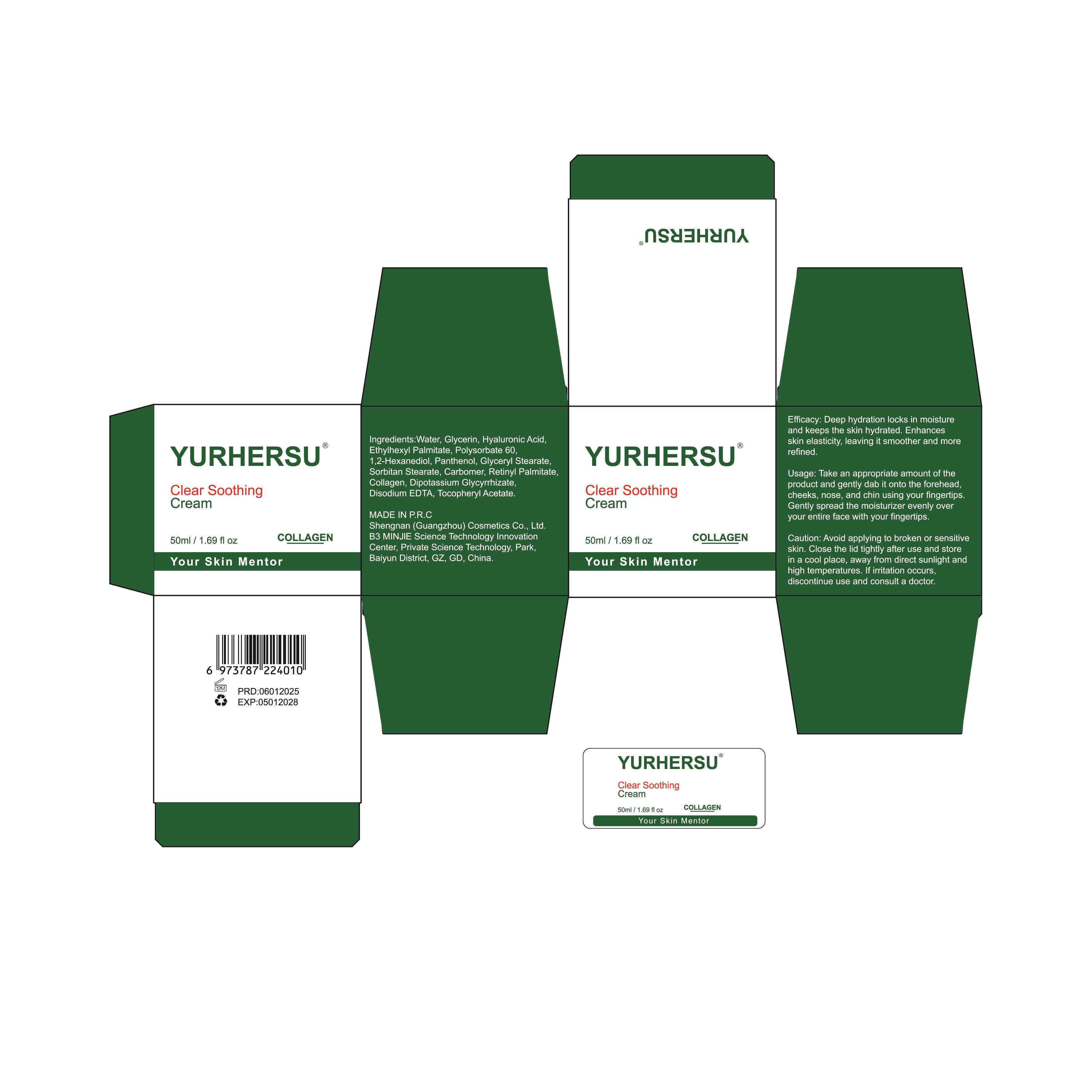 DRUG LABEL: ClearSoothingCream
NDC: 84019-023 | Form: CREAM
Manufacturer: Shengnan (Guangzhou) Cosmetics Co., LTD
Category: otc | Type: HUMAN OTC DRUG LABEL
Date: 20250103

ACTIVE INGREDIENTS: HYALURONIC ACID 100 mg/1 mL
INACTIVE INGREDIENTS: GLYCERIN; GLYCERYL STEARATE; DIPOTASSIUM GLYCYRRHIZATE; WATER; PANTHENOL; POLYSORBATE 60; SORBITAN STEARATE; ETHYLHEXYL PALMITATE; 1,2-HEXANEDIOL; CARBOMER

WARNINGS

Please keep out of reach of children.

PURPOSE

Deep hydration locks in moisture and keeps the skin hydrated. Enhances skin elasticity, leaving it smoother and morerefined.

STOP USE

lf irritation occurs.discontinue use and consult a doctor

ACTIVE INGREDIENT

Retinyl Palmitate

WHEN USING

Please keep your skin dry before use to ensure the best results fromthe product.

INACTIVE INGREDIENT

Water
Glycerin
Hyaluronic Acid
Ethylhexyl Palmitate
Polysorbate 60
1,2-Hexanediol
Panthenol
Glyceryl Stearate
Sorbitan Stearate
Carbomer
Collagen
Dipotassium Glycyrrhizate
Disodium EDTA
Tocopheryl Acetate

DOSAGE AND ADMINISTRATION

Apply 1-2 times a day

INDICATIONS AND USAGE

Take an appropriate amount of theproduct and gently dab it onto the forehead.cheeks, nose, and chin using your fingertips.Gently spread the moisturizer evenly overyour entire face with your fingertips